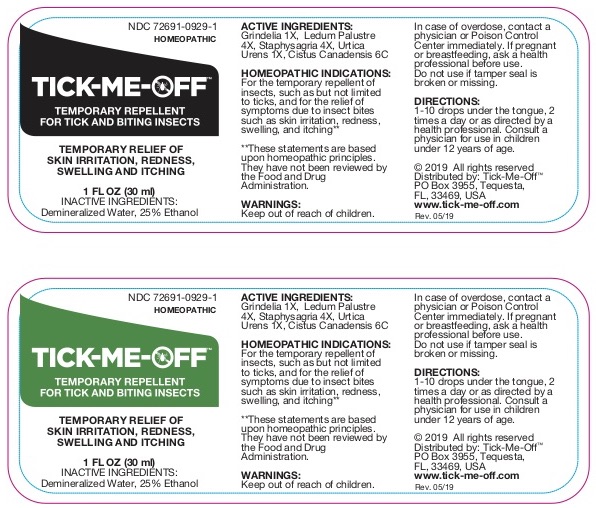 DRUG LABEL: Tick-Me-Off
NDC: 72691-0929 | Form: LIQUID
Manufacturer: PILLAR HEALTH SYSTEMS LLC
Category: homeopathic | Type: HUMAN OTC DRUG LABEL
Date: 20190708

ACTIVE INGREDIENTS: GRINDELIA HIRSUTULA WHOLE 1 [hp_X]/1 mL; URTICA URENS 1 [hp_X]/1 mL; LEDUM PALUSTRE TWIG 4 [hp_X]/1 mL; DELPHINIUM STAPHISAGRIA SEED 4 [hp_X]/1 mL; HELIANTHEMUM CANADENSE 6 [hp_C]/1 mL
INACTIVE INGREDIENTS: WATER; ALCOHOL

Tick-Me-Off

ACTIVE INGREDIENTS:

Grindelia 1x, Ledum Palustre 4x, Staphysagria 4x, Urtica Urens 1x, Cistus Canadensis 6C

HOMEOPATHIC INDICATIONS:

For the temporary repellent of insects, such as but not limited to ticks, and the relief of symptoms due to insect bites such as skin irritation, redness, swelling, and itching.**

**These statements are based upon traditional homeopathic principles. They have not been reviewed by the Food and Drug Administration.

WARNINGS:

If pregnant or breast-feeding, ask a health professional before use.

Do not use if tamper seal is broken or missing.

Keep out of reach of children. In case of overdose, contact a physician or Poison Control Center right away.

DIRECTIONS:

1-10 drops under the tongue, 2 times a day or as directed by a health professional. Consult a physician for use in children under 12 years of age.

HOMEOPATHIC INDICATIONS:

For the temporary repellent of insects, such as but not limited to ticks, and the relief of symptoms due to insect bites such as skin irritation, redness, swelling, and itching.**

**These statements are based upon traditional homeopathic principles. They have not been reviewed by the Food and Drug Administration.

INACTIVE INGREDIENTS:

Demineralized Water, 25% Ethanol.

QUESTIONS:

Distributed by: Tick-Me-Off®

PO Box 3955
Tequesta, FL, 33469

www-tick-me-off.com

PACKAGE LABEL DISPLAY:

NDC 72691-0929-1

HOMEOPATHIC

Tick-Me-Off®

1 FL OZ (30 ml)